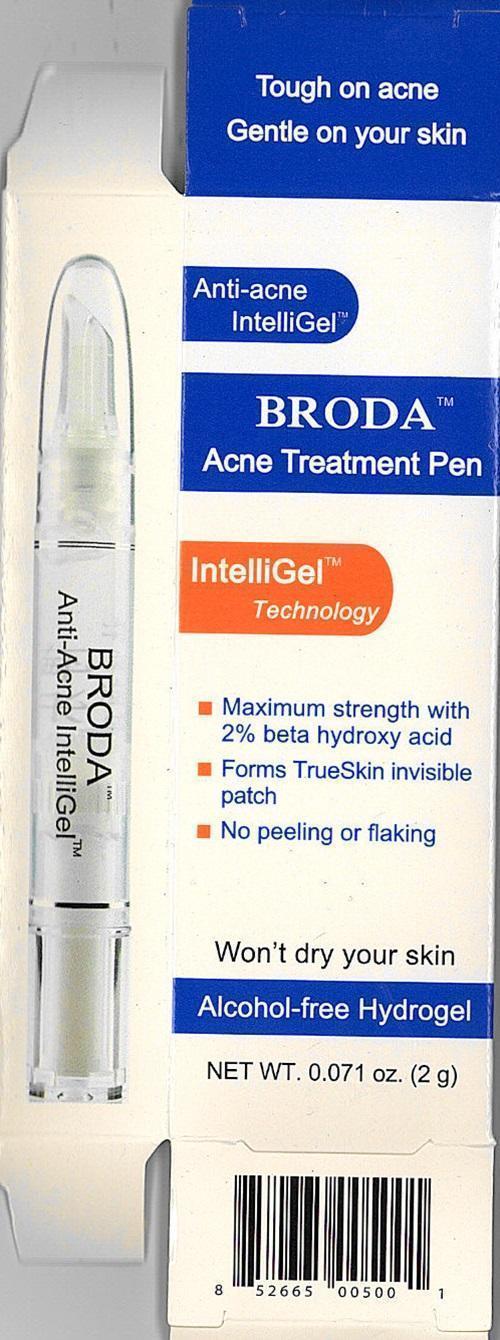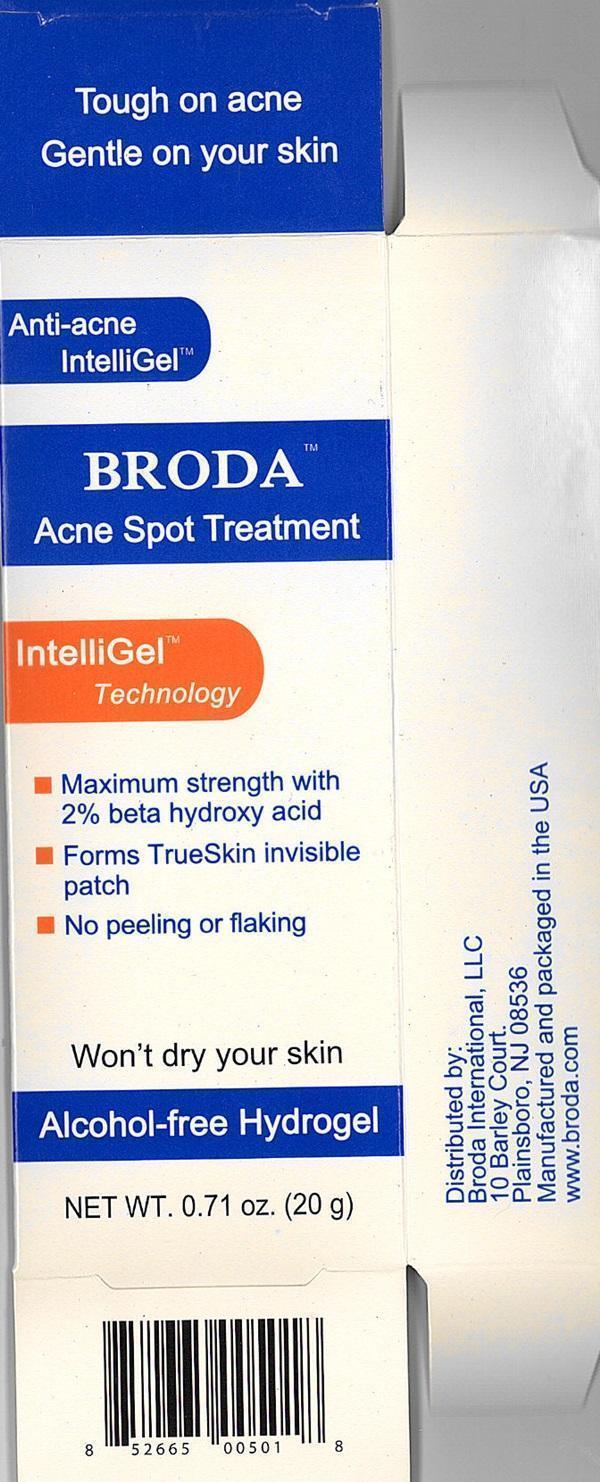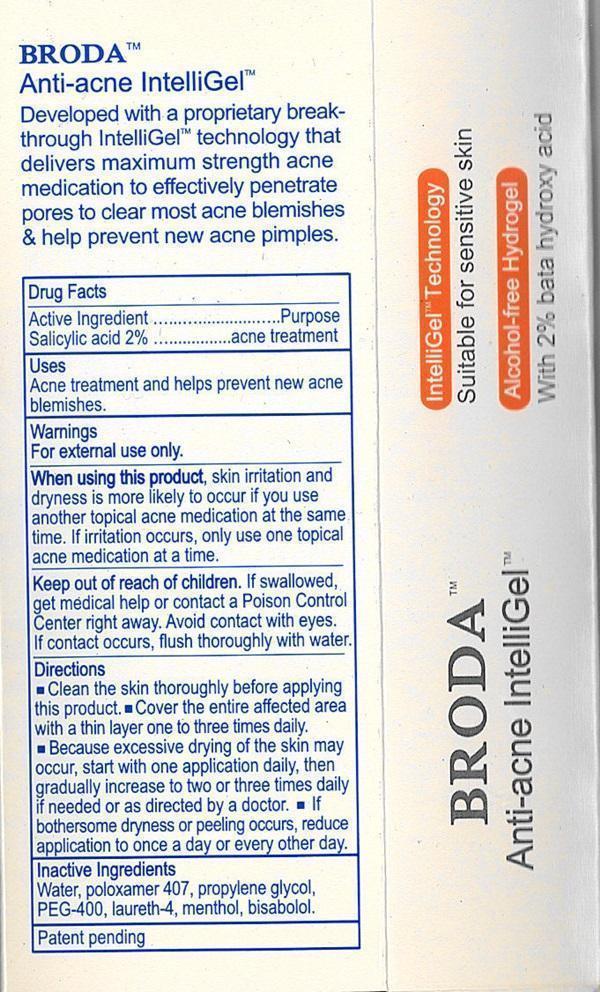 DRUG LABEL: BRODA Acne
                
NDC: 54111-112 | Form: GEL
Manufacturer: Bentley Laboratories, LLC
Category: otc | Type: HUMAN OTC DRUG LABEL
Date: 20241227

ACTIVE INGREDIENTS: SALICYLIC ACID 0.4 g/20 g
INACTIVE INGREDIENTS: WATER; POLOXAMER 407; PROPYLENE GLYCOL; POLYETHYLENE GLYCOL 400; LAURETH-4; MENTHOL; LEVOMENOL

Drug Facts Active Ingredient

Salicylic acid 2%

Purpose

acne treatment

Keep out of reach of children

If swallowed, get medical help or contact a Poison Control Center right away.

Uses

Acne treatment and helps prevent new acne blemishes.

Warnings

For external use only.

When using this product

skin irritation and dryness is more likely to occur if you use another topical acne medication at the same time. If irritation occurs, only use one topical acne medication at a time.
Avoid contact with eyes. If contact occurs, flush thoroughly with water.

Directions

- Clean the skin thoroughly before applying this product.
- Cover the entire affected area with a thin layer one to three times daily.
- Because excessive drying of the skin may occur, start with one application daily, then gradually increase to two or three times daily if needed or as directed by a doctor.
- If bothersome dryness or peeling occurs, reduce application to once a day or every other day

Inactive ingredients

Water, poloxamer 407, propylene glycol, PEG-400, laureth-4, menthol, bisabolol.

BRODA Acne Spot Treatment and Acne Treatment Pen Labels

Tough on acne
Gentle on your skin
Anti-acne IntelliGel™
BRODA Acne Spot Treatment

Broda Acne Treatment Pen

IntelliGel™ Technology
Suitable for sensitive skin

Maximum strength with 2% beta hydrox acid
Forms TrueSkin invisible patch
No peeling or flaking

Won't dry your skin

Alcohol-free Hydrogel
NET WT. 0.071 oz. (2g) - 0.71 oz. (20 g)
Distributed by:
Broda International, LLC
10 Barley Court
Plainsboro, NJ 08536
Manufactured and packaged in the USA
www.broda.com
Patent pending
BRODA™
Anti-acne IntelliGel™
Developed with a proprietary break-through IntellGel™ technology that delivers maximum strength acne medication to effectively penetrate pores to clear most acne blemishes and help prevent new acne pimples.

res